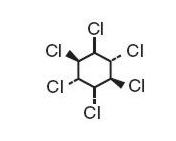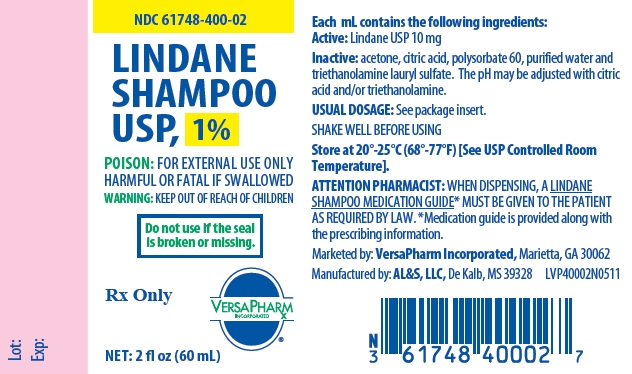 DRUG LABEL: Lindane
NDC: 61748-400 | Form: SHAMPOO
Manufacturer: VersaPharm Incorporated
Category: prescription | Type: HUMAN PRESCRIPTION DRUG LABEL
Date: 20111213

ACTIVE INGREDIENTS: LINDANE 10 mg/1 mL
INACTIVE INGREDIENTS: ACETONE; ANHYDROUS CITRIC ACID; POLYSORBATE 60; WATER; TROLAMINE LAURYL SULFATE

LINDANE SHAMPOO USP, 1%

Rx only

WARNINGS

Lindane Shampoo should only be used in patients who cannot tolerate or have failed first-line treatment with safer medications for the treatment of lice. (See INDICATIONS AND USAGE.)

Neurologic Toxicity

Seizures and deaths have been reported following Lindane Shampoo use with repeat or prolonged application, but also in rare cases following a single application according to directions. Lindane Shampoo should be used with caution in infants, children, the elderly, and individuals with other skin conditions, and those who weigh < 110 lbs (50 kg) as they may be at risk of serious neurotoxicity.

Contraindications

Lindane Shampoo is contraindicated in premature infants and individuals with known uncontrolled seizure disorders.

Proper Use

Instruct patients on proper use of Lindane Shampoo, the amount to apply, how long to leave it on, and avoiding retreatment. Inform patients that itching occurs after the successful killing of lice and is not necessarily an indication for retreatment with Lindane Shampoo. (See DOSAGE AND ADMINISTRATION.)

DESCRIPTION

Lindane Shampoo USP, 1%, is an ectoparasiticide and ovicide effective against Pediculosis humanis capitis (head lice), Pthirus pubis (crab lice), and their ova. In addition to the active ingredient, lindane, it contains acetone, citric acid, polysorbate 60, purified water and triethanolamine lauryl sulfate to form a shampoo base. The pH may be adjusted with citric acid and/or triethanolamine. Lindane is the gamma isomer of 1,2,3,4,5,6-hexachlorocyclohexane having the following structural formula:

C6H6Cl6 M.W. 290.83

CLINICAL PHARMACOLOGY

Lindane exerts its parasiticidal action by being directly absorbed into the parasites and their ova. Feldmann and Maibach^1 reported approximately 10% absorption of a lindane acetone solution applied to the forearm of human subjects and left in place for 24 hours. This vehicle was different from the approved product and the percutaneous penetration of lindane is dependent on the vehicle. Therefore, the clinical significance of these observations is unknown. Dale, et al^2 reported a blood level of 290 ng/mL associated with convulsions following the accidental ingestion of a lindane-containing product. Ginsburg^3 found a mean peak blood level of 28 ng/mL 6 hours after total body application of Lindane Lotion to scabietic infants and children. The half-life in blood was determined to be 18 hours.

Data available in the literature suggest that lindane has a rapid distribution phase followed by a longer β-elimination phase.^1,2,3

There are no clinical dose ranging studies for Lindane Shampoo.

INDICATIONS AND USAGE

Lindane Shampoo is indicated for the treatment of head lice (infestations of Pediculosis humanis capitis), crab lice (infestations of Pthirus pubis), and their ova only in patients who

1. cannot tolerate other approved therapies, or
2. have failed treatment with other approved therapies.

Lindane Shampoo should be used in the context of an overall lice management program that includes:

- Visual inspection to ensure that the patient is currently infested with live lice (empty egg casings or "nits" can remain on hair shaft long after true infestation).
- Manual removal of nits using a comb designed for this purpose and/or individual removal with tweezers followed by close examination of the hair and scalp.
- Evaluation and treatment of sexual contacts simultaneously. Sexual contacts should be prescribed Lindane Shampoo only if they either have failed to respond to adequate doses of other approved therapies or are intolerant of other approved therapies.
- All recently worn clothing, underwear, pajamas, used sheets, pillowcases, and towels should be washed in very hot water or dry-cleaned.

Caregivers applying this product to patients should wear gloves less permeable to Lindane such as nitrile, latex with neoprene or sheer vinyl, and thoroughly clean hands after application. Natural latex gloves should be avoided because they are more permeable to Lindane.

Lindane Shampoo does not prevent infestation or reinfestation and should not be used to ward off a possible infestation.

CONTRAINDICATIONS

Lindane Shampoo is contraindicated for premature infants because their skin may be more permeable than that of full term infants and their liver enzymes may not be sufficiently developed to metabolize Lindane.

Lindane Shampoo is also contraindicated for patients with crusted (Norwegian) scabies and other skin conditions (e.g., atopic dermatitis, psoriasis) that may increase systemic absorption of the drug.

Lindane Shampoo is contraindicated for patients with known uncontrolled seizure disorders and for individuals with a known sensitivity to the product or any of its components.

WARNINGS

(See boxed WARNINGS.)

Seizures and deaths have been reported following Lindane Shampoo use with repeat or prolonged application, but also in rare cases following a single application according to directions.

There have been cases of adverse events reported for Lindane Shampoo and Lindane Lotion in which a serious outcome (hospitalization, disability or death) has occurred.^4 In approximately 20% of these cases, the shampoo and lotion were reported to have been used according to the labeled directions. Of these cases, thirteen deaths were reported, many of which were remote from the time of actual Lindane use. Lindane toxicity, verified by autopsy was the cause of one infant's death, and was the cause of death reported for an adult in a successful suicide. The direct causes of death for the other cases were attributed to reasons other than lindane. Most of these adverse events occurred with Lindane Lotion.

Infants, children, the elderly, and individuals with other skin conditions and those who weigh < 110 lbs (50 kg) may be at a greater risk of serious neurotoxicity. (See Pediatric Use and Geriatric Use.) Animal studies have shown increased susceptibility to neurologic adverse events in younger animals. Children have a larger body surface area to volume ratio that may result in a proportionately larger systemic exposure.

Careful consideration should be given before prescribing Lindane Shampoo to patients with conditions that may increase the risk of seizure, such as HIV infection, history of head trauma or a prior seizure, CNS tumor, the presence of severe hepatic cirrhosis, excessive use of alcohol, abrupt withdrawal from alcohol or sedatives, as well as concomitant use of medications known to lower seizure threshold. (See PRECAUTIONS: Drug Interactions.)

Patients should be instructed on the proper use of Lindane Shampoo, especially the amount to apply, how long to leave shampoo on, and the need to avoid retreatment. Patients should be informed that itching may occur after the successful killing of lice and repeat treatment may not be necessary.

A Lindane Shampoo Medication Guide must be given to the patient each time Lindane Shampoo is dispensed, as required by law.

PRECAUTIONS

General

Care should be taken to avoid contact with the eyes. If such contact occurs, eyes should be immediately flushed with water. If irritation or sensitization occurs, the patient should be advised to consult a physician.

Information for Patients (and Caregivers)

- This product can be poisonous if misused.
- Other important information is found in the Medication Guide, which by law, must be dispensed with Lindane Shampoo.
- If putting Lindane Shampoo on another person, the person applying shampoo should wear less permeable gloves such as nitrile, latex with neoprene, or sheer vinyl, and thoroughly clean their hands after application. Natural latex should be avoided because it is more permeable to lindane.
- If the person applying Lindane Shampoo could be pregnant, contact with Lindane Shampoo should be avoided as much as possible.
- If the patient could be pregnant, other treatments may be preferable.
- Use Lindane Shampoo for lice only.
- The use of oil treatments, oil based hair dressings or conditioners immediately before and after applying Lindane Shampoo should be avoided. Oils can make the Lindane Shampoo go through the skin faster and possibly increase the risk of neurotoxicity (e.g., seizures).
- Information for Use
  - Shake Lindane Shampoo well.
  - Hair should be completely dry prior to application of Lindane Shampoo.
  - Use only enough Lindane Shampoo to lightly coat the hair and scalp.
  - Apply shampoo directly to dry hair without adding water. Work thoroughly into the hair and allow to remain in place for 4 minutes only. Special attention should be given to the fine hairs along the neck and behind the ears.
  - After 4 minutes, add small quantities of water to hair until a good lather forms.
  - Immediately rinse all lather away. Avoid unnecessary contact of lather with other body surfaces.
  - Towel briskly and then remove nits with nit comb or tweezers.
  - There may be some Lindane Shampoo left in the bottle. Close the bottle with the leftover Lindane Shampoo and immediately throw away the bottle in a trash can out of the reach of children.
  - Do not cover the hair with anything that does not breathe, like a shower cap or towel.
  - Do not ingest. Keep away from mouth and eyes. If contact with eyes occurs, immediately flush eyes with water. Do not use if open wounds, cuts or sores are present, unless specifically directed by your physician.
  - Wash all recently worn clothing, underwear and pajamas, hats, and used sheets, pillowcases, and towels in very hot water or dry-clean.
  - Patients may still itch after using Lindane Shampoo. This does not mean the medicine did not work. Lindane Shampoo sometimes makes this itch even worse. Other medications can be used to soothe the itch. Do not use more Lindane Shampoo.
  - If there are any questions or concerns about the condition or use of the Lindane Shampoo, contact your physician.

Drug Interactions

Oils may enhance absorption of lindane, therefore, patients and caregivers applying the shampoo to others should avoid using oil treatments, or oil-based hair dressings or conditioners immediately before and after applying Lindane Shampoo.

In addition, there are many drugs that may lower the seizure threshold, and Lindane Shampoo should be prescribed with caution in patients taking these medications. Drugs that may lower the seizure threshold include, but are not limited to the following:

- Antipsychotics
- Antidepressants
- Theophylline
- Cyclosporine, mycophenolate mofetil, tacrolimus capsules
- Penicillins, imipenem, quinolone antibiotics
- Chloroquine sulfate, pyrimethamine
- Isoniazid
- Meperidine
- Radiographic contrast agents
- Centrally active anticholinesterases
- Methocarbamol

Carcinogenesis, Mutagenesis, and Fertility

Although no studies have been conducted with Lindane Shampoo, numerous long-term feeding studies have been conducted in mice and rats to evaluate the carcinogenic potential of the technical grade of hexachlorocyclohexane as well as the alpha, beta, gamma (lindane) and delta isomers. Both oral and topical applications have been evaluated. Increased incidences of neoplasms were not clearly related to administration of lindane. The results of mutagenicity tests in bacteria do not indicate that lindane is mutagenic. Lindane did not cause sister chromatid exchange in an in vivo assay. The number of spermatids in the testes of rats 2 weeks after oral administration of a single dose of 30 mg/kg body weight (12 times the estimated human exposure for scabies on a body surface area comparison and assuming 50% rat oral bioavailability and 10% human bioavailability) was significantly reduced compared to the control rats.

Pregnancy

Pregnancy Category C

All pregnancies have a risk of birth defect, loss, or other adverse event regardless of drug exposure. Predictions of fetal risk from drug exposure rely heavily on animal data. However, animal studies may fail to predict effects in humans or may overstate such risks. Even if human data are available, the data may not be sufficient to determine whether there is an increased risk to the fetus, and individual reports of adverse outcomes in pregnancy in association with a drug may not reflect a causal relationship.

Lindane Shampoo should be given to pregnant women only if clearly needed. There are no adequate and well-controlled studies of Lindane Shampoo in pregnant women. There are no known maternal or fetal health risks described if lice are not treated, but risk of transmission of the lice to other household members is an additional consideration when deciding whether to use lice treatments. Lindane is lipophilic and may accumulate in the placenta. There has been a single case report of a stillborn infant following multiple maternal exposures during pregnancy to Lindane Lotion. The relationship of the maternal exposures to the fetal outcome is unknown.

Animal data suggest that lindane may increase the likelihood of neurologic developmental abnormalities (see below), based on findings at systemic exposures close to that expected in humans when Lindane Lotion is used to treat scabies. The immature central nervous system (as in the fetus) may have increased susceptibility to the effects of the drug. Systemic exposure resulting from Lindane Shampoo applied to hair covered areas is expected to be lower than that from Lindane Lotion that covers the entire body surface area.

Data

When rats received lindane in the diet from day 6 of gestation through day 10 of lactation, reduced pup survival, decreased pup weight and decreased weight gains during lactation, increased motor activity and decreased motor activity habituation were seen in pups at 5.6 mg/kg (2 times the estimated human exposure) but not at 1.2 mg/kg. An increased number of stillborn pups was seen at 8 mg/kg, and increased pup mortality was seen at 5.6 mg/kg. No gross abnormalities were seen in this study or in a study in which rabbits received up to 20 mg/kg lindane by gavage on gestation day 6–18 (up to 10 times the human exposure on a body surface area comparison and assuming 50% rabbit oral bioavailability and 10% human bioavailability when lindane is applied to the entire body for the treatment of scabies).

Nursing Mothers

Lindane is lipophilic and is present in human breast milk, but exact quantities are not known. There may be a risk of toxicity if lindane is ingested from breast milk, or from skin absorption from mother to baby in the course of breast-feeding if Lindane Shampoo is applied topically to the chest area. Nursing mothers who require treatment with Lindane Shampoo should be advised of the potential risks and be instructed not to use the product on the skin as would be done for treatment of scabies. They should also be counseled to interrupt breast-feeding, with expression and discarding of milk, for at least 24 hours following use.

Pediatric Use

Animal data demonstrated increased risk of adverse events in the young across species. Pediatric patients have a higher surface to volume ratio and may be at risk of greater systemic exposure when Lindane Shampoo is applied. Infants and children may be at an even higher risk due to immaturity of organ systems such as skin and liver. Lindane Shampoo should be used with caution in patients who weigh less than approximately 110 lbs (50 kg) and especially in infants. Lindane Shampoo is indicated only for the treatment of lice; patients with scabies should use Lindane Lotion according to the labeled instructions.

Geriatric Use

There have been no studies of Lindane Shampoo in the elderly. There are four postmarketing reports of deaths in elderly patients treated with Lindane Lotion for the indication of scabies. Two patients died within 24 hours of Lindane Lotion application, and the third patient died 41 days after application of Lindane Lotion, having suffered a seizure on the day of death. A fourth patient died of an unreported cause of death on the same day that Lindane Lotion treatment for scabies was administered.

ADVERSE REACTIONS

Central nervous system stimulation ranging from dizziness to seizures, has been reported particularly with use of Lindane Lotion. Although seizures were almost always associated with ingestion or misuse of the product (to include repeat treatment), seizures and deaths have been reported when Lindane Shampoo was used according to directions. Irritant dermatitis from contact with this product has also been reported. (See WARNINGS, PRECAUTIONS, and DOSAGE AND ADMINISTRATION.)

Postmarketing Experience

The following adverse reactions reflect the additional postmarketing experience of Lindane Shampoo. These events include alopecia, dermatitis, headache, pain, paresthesia, pruritus and urticaria. The relationship of some of these events to lindane therapy is unknown.

OVERDOSAGE

Contact the closest Poison Control Center in the event of suspected overdosage with Lindane Shampoo.

If accidental ingestion occurs, prompt gastric lavage should be instituted. However, since oils enhance absorption, saline cathartics for intestinal evacuation should be given rather than oil laxatives. If central nervous system manifestations occur, they may be antagonized by the administration of pentobarbital, phenobarbital, or diazepam.

DOSAGE AND ADMINISTRATION

Most patients will require only 1 ounce of Lindane Shampoo. Based on the length and density of hair, some patients may require 2 ounces of Lindane Shampoo.

Apply shampoo directly to dry hair without adding water. Work thoroughly into the hair and allow to remain in place for 4 minutes only. Special attention should be given to the fine hairs along the neck. After 4 minutes, add small quantities of water to hair until a good lather forms. Immediately rinse all lather away. Avoid unnecessary contact of lather with other body surfaces. Do not prescribe more than 2 ounces for larger adults. Do not retreat. (See boxed WARNINGS.)

Patients should be provided specific information on use of product. (See PRECAUTIONS: Information for Patients and Lindane Shampoo Medication Guide.)

A Lindane Shampoo Medication Guide must be given to the patient each time LINDANE Shampoo is dispensed as required by law. The Lindane Shampoo Medication Guide is an important part of the risk management program for the patient.

HOW SUPPLIED

Lindane Shampoo USP, 1% is supplied in 2 fl oz (60 mL) NDC 61748-400-02 bottles.

SHAKE WELL BEFORE USING

STORAGE AND HANDLING

Store at 20°-25°C (68°-77°F) [See USP Controlled Room Temperature].

REFERENCES

1. Feldmann, R.J. and Maibach, H.I., Toxicol. Applied. Pharmacol., 28:126, 1974.
2. Dale, W.E., Curly, A. and Cueto, C. Life Sci 5:47, 1966.
3. Ginsburg, C.M., et al., J. Pediatr. 91:6, 998–1000, 1977.
4. FDA AERS database search, January 2003

Manufactured by:

AL&S, LLC

De Kalb, MS 39328

Marketed by:

VersaPharm Incorporated

Marietta, GA 30062

IVP40002-00

Issued: 05-24-2011

PHARMACIST—PATIENT MEDICATION GUIDE PROVIDED BELOW

MEDICATION GUIDE

Lindane (LIHN-dane) Shampoo USP, 1%

You must read and follow all instructions before using Lindane Shampoo. Read the information you get every time you or a family member get Lindane Shampoo. There may be new information. This Medication Guide does not take the place of talking with your doctor about your medical condition or treatment. If you have any questions about Lindane Shampoo, ask your doctor or pharmacist.

What is the most important information I should know about Lindane Shampoo?

Lindane Shampoo is a poison if you do not use it the right way. Lindane Shampoo goes through your skin and can affect your brain and nerves. Lindane Shampoo can cause seizures, also called convulsions, "fits" or epilepsy.

- Seizures and death can happen in people who use Lindane Shampoo too much or too often.
- Seizures can happen in some people even if they use Lindane Shampoo exactly as directed.

If you or a family member has a seizure while using Lindane Shampoo, get emergency help right away.

- Do not use Lindane Shampoo unless
  - You have lice and another medicine did not work for you, or
  - You cannot use other, safer medicines to treat your lice
- Do not use Lindane Shampoo more than 1 time to treat an attack of lice. Do not use Lindane Shampoo to treat a second attack that comes soon after the first episode. No one knows a safe time to reuse Lindane Shampoo. Even if you still itch even after using Lindane Shampoo, do not use more or use it again. Lice (bugs) can make you itch for some time even after all of the bugs are dead.
- Do not use more Lindane Shampoo than your doctor tells you.
- Do not keep Lindane Shampoo on your hair for more than 4 minutes.
- Do not put Lindane Shampoo in your mouth because it is a poison if taken by mouth. If you get Lindane Shampoo in your mouth or swallow Lindane Shampoo, call your area Poison Control Center right away and get emergency help.

What is Lindane Shampoo?

Lindane Shampoo is a medicine that is used to treat lice. It kills lice and their eggs. Lice are very small bugs that attach to the skin on your head or pubic (crotch) area and lay eggs called nits in your hair. Some people call crotch lice "crabs". Lice can cause severe itching. Lindane Shampoo gets into the lice and the nits and kills them. It also goes through your skin. Lindane Shampoo is used only after safer medicines have not made your lice go away. The only time Lindane Shampoo is used first is when someone cannot use safer medicines, which may include permethrin and crotamiton.

Lindane Shampoo is mainly for adults and children who weigh at least 110 pounds. If you weigh less than 110 pounds use Lindane Shampoo only if your doctor thinks it is really needed. People who weigh less than 110 pounds and the elderly have higher chances for side effects because more Lindane may go through their skin.

Who should not use Lindane Shampoo?

Do not use Lindane Shampoo:

- if you do not have lice. Lindane Shampoo does not stop you from getting lice. Lindane Shampoo only kills the lice you already have.
- if you have or have ever had seizures, also called convulsions, "fits" or epilepsy, especially if they have been hard to control.
- if you have used Lindane Shampoo in the past few months. You should see your doctor if you think that you need another treatment.
- unless it is the only medicine you can use for lice.
- if you had a bad reaction to Lindane Shampoo before. Do not use Lindane Shampoo again.
- if you have open sores or crusted (scabby) sores on the skin around your head and neck, or lots of broken skin.
- if you need to treat a premature or young baby. More of the applied Lindane can go through the skin of babies and go to their brains where it can harm them.
- if you have scabies. These need a different medicine that you use in a different way.
- if you are allergic to Lindane Shampoo or any of its ingredients. The active ingredient is lindane. See the end of this Medication Guide for a list of all the ingredients in Lindane Shampoo.
- while you are breast-feeding. Lindane Shampoo can get in your milk and may be fed to your baby. Your baby may get sick. Ask your doctor for a safer medicine. If you use Lindane Shampoo, pump your breast milk and throw the milk away for at least 24 hours after using the medicine. During this time, feed your baby formula or breast milk that you stored from before you used Lindane Shampoo.

Tell your doctor if you:

- used Lindane Shampoo in the past few months.
- ever had a seizure or problem that could increase your chances of getting a seizure (like a head injury, tumor in your brain or spinal cord, cirrhosis of the liver, or heavy alcohol drinking.)
- have HIV or AIDS. Lindane Shampoo may cause seizures even if you never had them before.
- are pregnant. Lindane Shampoo can reach your baby and may harm it. Ask your doctor for a safer medicine. Use Lindane Shampoo only if needed.
- have a sexual partner and your lice (crabs) are in your pubic (crotch) area. Your partner should get checked and treated for lice so they don't give them back to you. Don't share your Lindane Shampoo with your partner.

Tell your doctor about all the medicines you take, including prescription and non-prescription medicines, vitamins, and herbal supplements. Some medicines may increase your chances of having a seizure if you take them while using Lindane Shampoo. Especially tell your doctor if you take medicines called sedatives (drugs to help you sleep).

How do I use Lindane Shampoo?

Before you put it on:

- Make sure you know how to use it exactly as your doctor prescribes.
- If you are putting Lindane Shampoo on another person, wear special gloves made of nitrile, latex with neoprene, or sheer vinyl. Do not use natural latex gloves because more Lindane can go through that kind of glove. Keep the gloves on until the Lindane Shampoo is washed out of your hair. Wash your hands well when you are done.
- Make sure your hair and skin on your head and neck do not have any other shampoo, cream, or oil on it. Oils can make the Lindane Shampoo go through your skin faster and may increase the risk of seizures.

When you put it on:

- Shake the bottle of Lindane Shampoo well.
- Make sure your hair is clean and dry before using Lindane Shampoo, but do not wash your hair within 1 hour before using Lindane Shampoo. Use regular shampoo without conditioner and dry your hair.
- Use just enough Lindane Shampoo on your dry hair to wet your hair and scalp. Do not add water to your hair at this time. Also, put Lindane Shampoo on the short hairs at the back of your neck.
- Keep Lindane Shampoo on your hair for 4 minutes. Use a watch or clock to time yourself.
- Do not wear a shower cap or any covering on your head while you wait for the 4 minutes to pass.
- Close the bottle with the leftover Lindane Shampoo and throw it away in a trash can out of the reach of children.

When you are supposed to wash it off:

- After 4 minutes has passed, soap up or lather the Lindane Shampoo. Use a small amount of warm water to do this. Hot water is not safe. Then wash the Lindane Shampoo off your head. Again, use warm, but not hot water. Do not leave any Lindane Shampoo on your head or hair. It will not kill more of the lice and may continue to go through your skin and cause serious problems, such as seizures.

After you wash off Lindane Shampoo:

- Dry your hair with a towel. Use a special comb called a nit comb or tweezers to remove the dead nits (lice eggs) from your hair. Someone else will probably have to do this for you.
- All recently worn clothing, underwear, pajamas, hats, used sheets, pillowcases, and towels should be washed in very hot water or dry-cleaned.
- Do not use Lindane Shampoo again. If you think you need to use it again, you must check with your doctor to find out if and when it is most safe.

You may still itch after you have used Lindane Shampoo. This does not mean you need more Lindane Shampoo. Even after all the lice (bugs) are dead, they can still make your skin itch for a long time. Lindane Shampoo sometimes makes this itch even worse. Talk to your doctor about things you can do to soothe the itch.

What should I avoid while using Lindane Shampoo?

- Do not get Lindane Shampoo in your eyes. If you do, rinse your eyes with water right away. Get medical help if your eyes keep hurting.
- Do not get Lindane Shampoo on your hands. Wear special gloves made of nitrile, latex with neoprene, or sheer vinyl. Do not use natural latex gloves. Wash your hands well when you are done.
- If you are pregnant, do not use Lindane Shampoo unless you have talked to your doctor about using it. Avoid putting Lindane Shampoo on others if you are pregnant. See the special glove advice above if you have to put Lindane Shampoo on others.
- Do not use oils on your skin or hair, just before or after using Lindane Shampoo. Oils include oil-based hair products and conditioners.

What are the possible side effects of Lindane Shampoo?

Lindane Shampoo may cause serious side effects such as seizures (convulsions, fits) or death (See the section, "What is the most important information I should know about Lindane Shampoo?"). Lindane Shampoo can also make you feel sleepy, dizzy, or can cause body shaking that you cannot control.

The most common side effects of Lindane Shampoo are:

- Itching skin
- Burning skin
- Dry skin
- A skin rash

These are not all of the possible side effects of Lindane Shampoo. For more information, ask your doctor or pharmacist.

General Information about Lindane Shampoo:

Medicines are sometimes prescribed for purposes other than those listed in Medication Guides. Do not use Lindane Shampoo for any condition for which it was not prescribed. Do not give Lindane Shampoo to other people, even if they have the same symptoms that you have. It may harm them. Keep Lindane Shampoo and all medicines out of the reach of children.

This Medication Guide summarizes the most important information about Lindane Shampoo. If you want more information, talk with your doctor. You can ask your doctor or pharmacist for information about Lindane Shampoo that is written for health professionals.

Call your doctor for medical advice about side effects. You may report side effects to FDA at 1800-FDA-1088.

What are the ingredients in Lindane Shampoo?

Active Ingredient: Lindane.

Inactive Ingredients: acetone, citric acid, polysorbate 60, purified water and triethanolamine lauryl sulfate.

This Medication Guide has been approved by the U.S. Food and Drug Administration.

Lindane is only available by a prescription from your doctor.

Manufactured by:

AL&S, LLC

De Kalb, MS 39328

Marketed by:

VersaPharm Incorporated

Marietta, GA 30062

GVP40002-00

Issued: 05-24-2011

PRINCIPAL DISPLAY PANEL- CONTAINER LABEL

NDC 61748-400-02

LINDANE

SHAMPOO

USP, 1%

POISON: FOR EXTERNAL USE ONLY

HARMFUL OR FATAL IF SWALLOWED

WARNING : KEEP OUT OF REACH OF CHILDREN

Do not use if the seal

is broken or missing.

Rx Only

NET: 2 fl oz (60 mL)